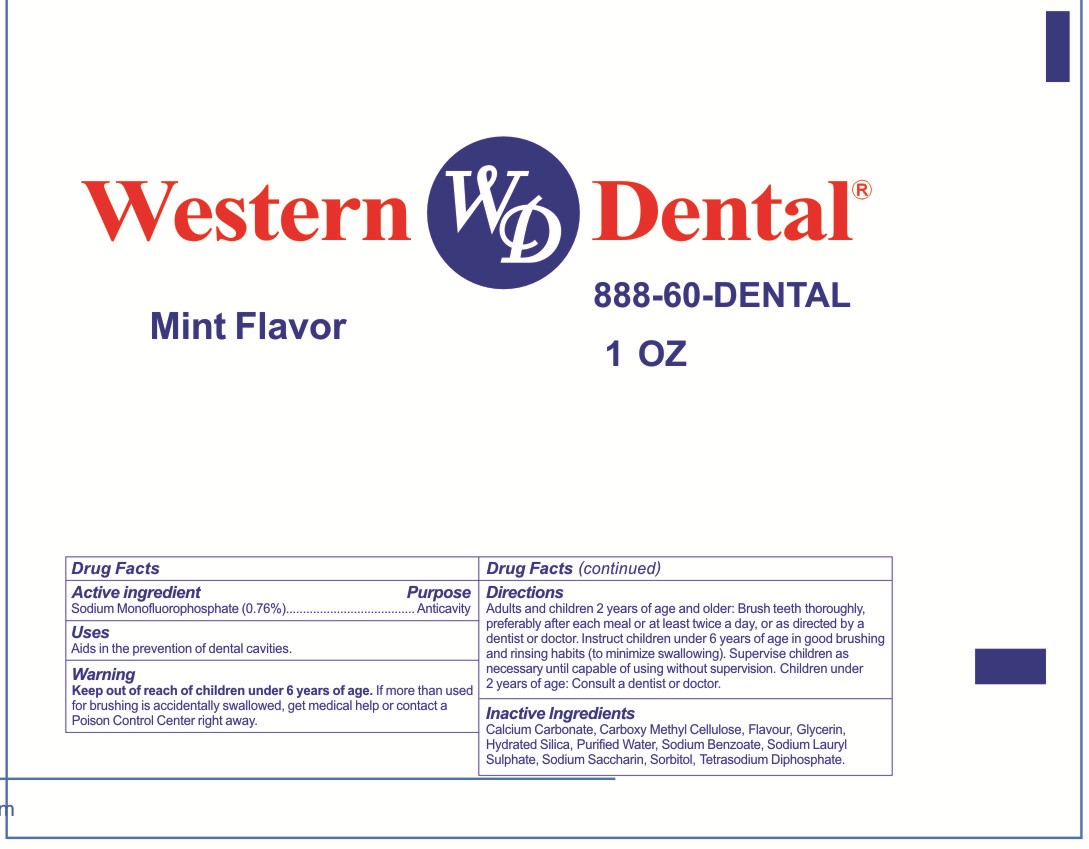 DRUG LABEL: Western  Dental
NDC: 71035-800 | Form: PASTE
Manufacturer: Yangzhou Hongshengding Chemical Co.,Ltd.
Category: otc | Type: HUMAN OTC DRUG LABEL
Date: 20170619

ACTIVE INGREDIENTS: SODIUM MONOFLUOROPHOSPHATE 0.76 g/100 g
INACTIVE INGREDIENTS: SODIUM LAURYL SULFATE; CALCIUM CARBONATE; CARBOXYMETHYLCELLULOSE; GLYCERIN; SACCHARIN SODIUM; WATER; HYDRATED SILICA; SODIUM BENZOATE; SORBITOL; PHYTONADIOL TETRASODIUM DIPHOSPHATE

Active ingredients

SODIUM MONOFLUOROPHOSPHATE 0.76%

Purpose

anticavity toothpaste

Uses

Aids in the prevention of dental cavities

Warnings

Keep out of the reach of children under 6 years of age.if more than used for brushing is accidentally swalowed, get medical help or contact a Poison Control Center right away.

Keep out of reach of children.

Directions

Adults and children 2years of age and older:Brush teeth thoroughly,preferably after each meal or at least twice a day,or as directed by a dentist or a doctor.

Instruct children under 6 years of age in good brushing and rinsing habits (to minimize swallowing),

supervise children as necessary until capable of useing without supervision.Children under 2 years of age:consult a dentist or doctor.

INACTIVE INGREDIENT

calcium carbonate,CarboxyMethyl Cellulose ,glycerin,hydrated silica,purified water,Sodium Benzoate,Sodium Lauryl Sulfate,Sodium Saccharin,Sorbitol,Tetrasodium Diphosphate